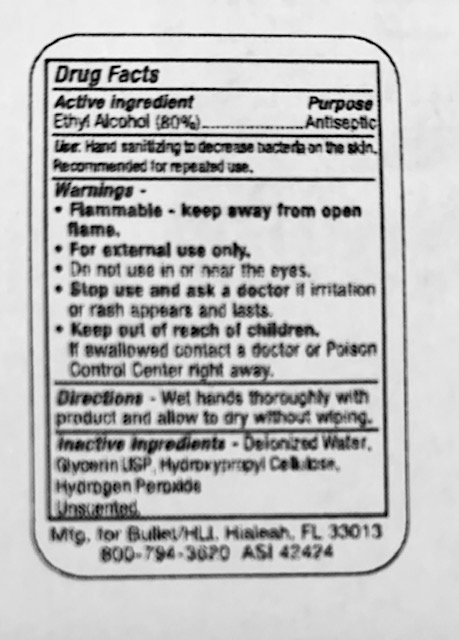 DRUG LABEL: Hand Sanitizer
NDC: 19392-230 | Form: GEL
Manufacturer: Bullet Line, LLC
Category: otc | Type: HUMAN OTC DRUG LABEL
Date: 20200821

ACTIVE INGREDIENTS: ALCOHOL 800 mL/1000 mL
INACTIVE INGREDIENTS: HYDROGEN PEROXIDE; WATER; HYDROXYPROPYL CELLULOSE, UNSPECIFIED; GLYCERIN

Drug Facts

ACTIVE INGREDIENT

Ethyl Alcohol (80%)

PURPOSE

Antiseptic

INDICATIONS AND USAGE

Hand sanitizer to help reduce bacteria on the skin. Recommended for repeated use.

WARNINGS

Flammable - keep away from open flame.

For external use only.

Do not use in or near the eyes.

Stop use and ask doctor if irritation or rash appears and lasts.

Keep out of reach of children.

If swallowed, contact a doctor or Poison Control Center right away.

INACTIVE INGREDIENT

Deionized Water, glycerin USP (glycerol), hydroxypropyl cellulose, hydrogen peroxide USP

Keep out of reach of children. If swallowed, contact a doctor or Poison Control center right away.

DOSAGE AND ADMINISTRATION

Wet hands thoroughly with product and allow to dry without wiping.